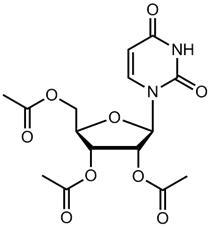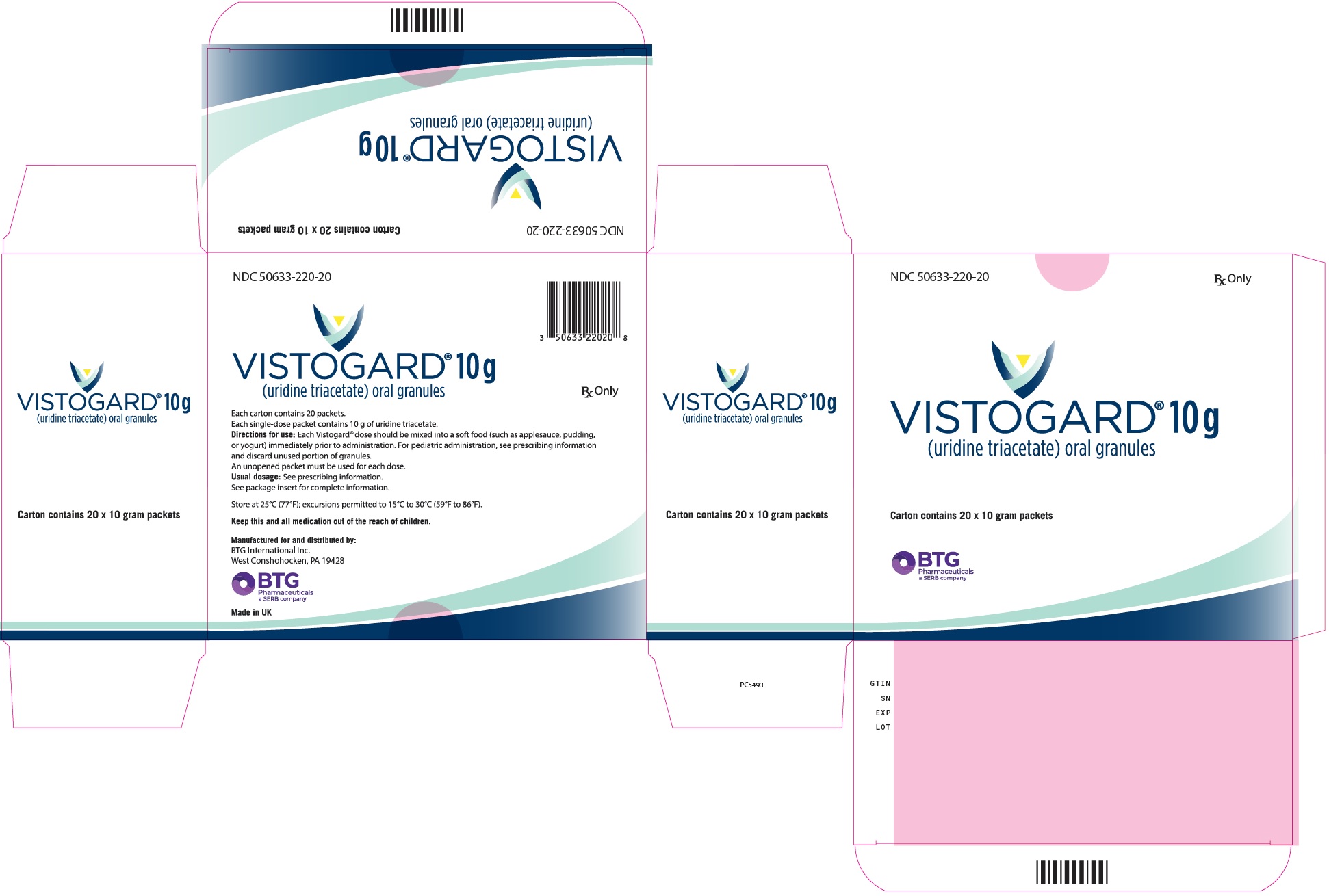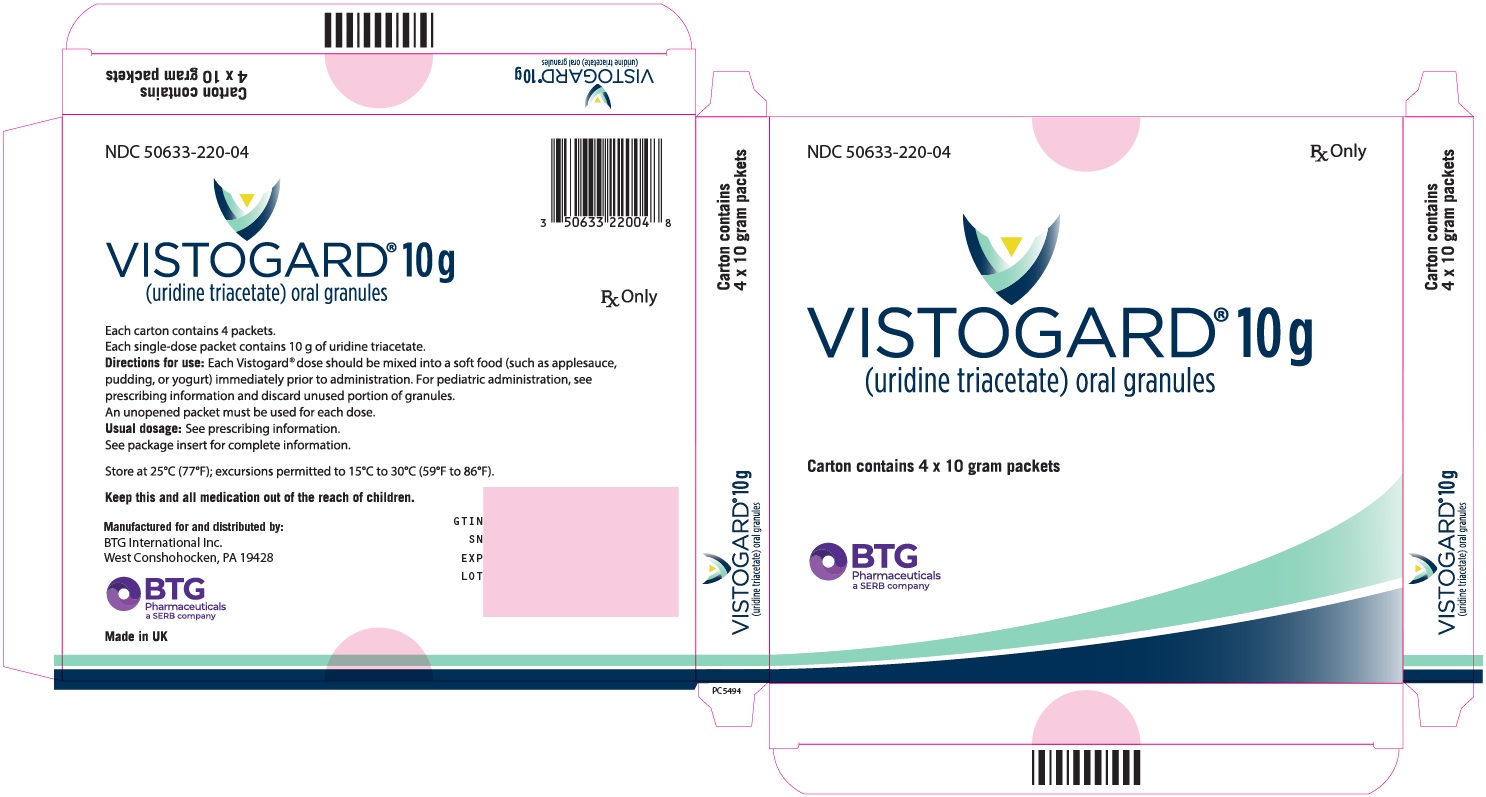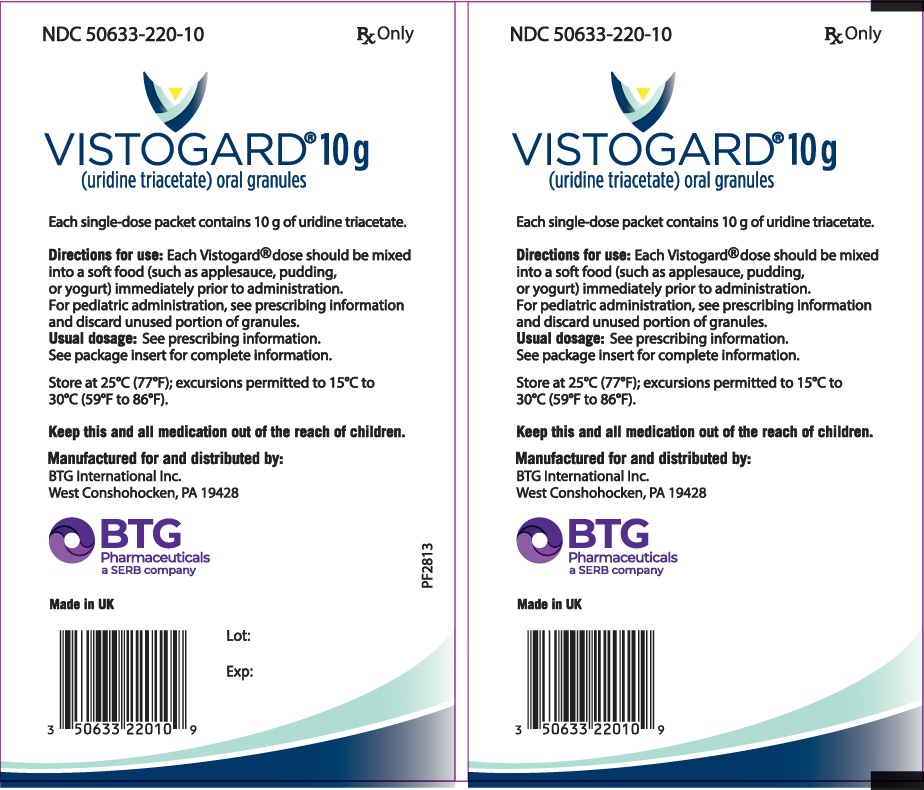 DRUG LABEL: VISTOGARD
NDC: 50633-220 | Form: GRANULE
Manufacturer: BTG International Inc
Category: prescription | Type: HUMAN PRESCRIPTION DRUG LABEL
Date: 20250207

ACTIVE INGREDIENTS: URIDINE TRIACETATE 951 mg/1 g
INACTIVE INGREDIENTS: ORANGE JUICE; HYPROMELLOSE, UNSPECIFIED; POLYETHYLENE GLYCOL, UNSPECIFIED; ETHYLCELLULOSE, UNSPECIFIED

HIGHLIGHTS OF PRESCRIBING INFORMATION

These highlights do not include all the information needed to use VISTOGARD safely and effectively. See full prescribing information for VISTOGARD.
VISTOGARD®(uridine triacetate) oral granules
Initial U.S. Approval: 2015

1 INDICATIONS AND USAGE

VISTOGARD ®is a pyrimidine analog indicated for the emergency treatment of adult and pediatric patients:

- following a fluorouracil or capecitabine overdose regardless of the presence of symptoms, or
- who exhibit early-onset, severe or life-threatening toxicity affecting the cardiac or central nervous system, and/or early-onset, unusually severe adverse reactions (e.g., gastrointestinal toxicity and/or neutropenia) within 96 hours following the end of fluorouracil or capecitabine administration. (1)

Limitations of use:

- VISTOGARD is not recommended for the non-emergent treatment of adverse reactions associated with fluorouracil or capecitabine because it may diminish the efficacy of these drugs. (1)
- The safety and efficacy of VISTOGARD initiated more than 96 hours following the end of fluorouracil or capecitabine administration have not been established. (1)

2 DOSAGE AND ADMINISTRATION

Recommended Dosage

- Adults: 10 grams (1 packet) orally every 6 hours for 20 doses, without regard to meals. (2.1)
- Pediatric: 6.2 grams/m^2of body surface area (not to exceed 10 grams per dose) orally every 6 hours for 20 doses, without regard to meals. See the full prescribing information for body surface area-based dosing. (2.1)

Preparation and Administration

- Pediatric: Measure the dose using either a scale accurate to at least 0.1 gram, or a graduated teaspoon accurate to ¼ teaspoon. (2.1)
- Mix each VISTOGARD dose with 3 to 4 ounces of soft foods such as applesauce, pudding or yogurt and ingest within 30 minutes of mixing. Do not chew the VISTOGARD granules. Drink at least 4 ounces of water. (2.2)
- If a patient vomits within 2 hours of taking a dose of VISTOGARD, initiate another complete dose as soon as possible after the vomiting episode. Administer the next dose at the regularly scheduled time. (2.2)
- If a patient misses a dose at the scheduled time, administer that dose of VISTOGARD as soon as possible. Administer the next dose at the regularly scheduled time. (2.2)
- Administer VISTOGARD via a nasogastric tube (NG tube) or gastrostomy tube (G-Tube) when necessary (e.g., severe mucositis or coma). (2.2)

3 DOSAGE FORMS AND STRENGTHS

Oral granules: 10 gram packets (3)

4 CONTRAINDICATIONS

None. (4)

5 WARNINGS AND PRECAUTIONS

None. (5)

6 ADVERSE REACTIONS

Adverse reactions occurring in >2% of patients receiving VISTOGARD included vomiting, nausea, and diarrhea. (6)

To report SUSPECTED ADVERSE REACTIONS, contact BTG International Inc at (1-877-377-3784) or FDA at 1-800-FDA-1088 or www.fda.gov/medwatch.

FULL PRESCRIBING INFORMATION

1 INDICATIONS AND USAGE

VISTOGARD ®is indicated for the emergency treatment of adult and pediatric patients:

- following a fluorouracil or capecitabine overdose regardless of the presence of symptoms, or
- who exhibit early-onset, severe or life-threatening toxicity affecting the cardiac or central nervous system, and/or early-onset, unusually severe adverse reactions (e.g., gastrointestinal toxicity and/or neutropenia) within 96 hours following the end of fluorouracil or capecitabine administration.

Limitations of Use

- VISTOGARD is not recommended for the non-emergent treatment of adverse reactions associated with fluorouracil or capecitabine because it may diminish the efficacy of these drugs.
- The safety and efficacy of VISTOGARD initiated more than 96 hours following the end of fluorouracil or capecitabine administration have not been established.

2 DOSAGE AND ADMINISTRATION

2.1 Recommended Dosage

- Adults: 10 grams (1 packet) orally every 6 hours for 20 doses, without regard to meals.
  Pediatric: 6.2 grams/m^2of body surface area (not to exceed 10 grams per dose) orally every 6 hours for 20 doses, without regard to meals. The VISTOGARD dose to be administered at 6.2 grams/m^2is presented in Table 1. Measure the dose using either a scale accurate to at least 0.1 gram, or a graduated teaspoon accurate to ¼ teaspoon. Discard any unused portion of granules. Do not use granules left in the open packet for subsequent dosing.
  Table 1 VISTOGARD Pediatric Dose Based on Body Surface Area (m^2)
  Patient Body Surface Area (m^2) | Table 1 VISTOGARD 6.2 grams/m^2/dose [Dose by body surface area category in this table was rounded to achieve the approximate dose. Each dose is administered every 6 hours for 20 doses.]
  Patient Body Surface Area (m^2) | Dose in Grams | Dose in Graduated Teaspoons
  0.34 to 0.44 | 2.1 to 2.7 | 1
  0.45 to 0.55 | 2.8 to 3.4 | 1 ¼
  0.56 to 0.66 | 3.5 to 4.1 | 1 ½
  0.67 to 0.77 | 4.2 to 4.8 | 1 ¾
  0.78 to 0.88 | 4.9 to 5.4 | 2
  0.89 to 0.99 | 5.5 to 6.1 | 2 ¼
  1.00 to 1.10 | 6.2 to 6.8 | 2 ½
  1.11 to 1.21 | 6.9 to 7.5 | 2 ¾
  1.22 to 1.32 | 7.6 to 8.1 | 3
  1.33 to 1.43 | 8.2 to 8.8 | 3 ¼
  1.44 and above [May use 1 entire 10 g packet without weighing or measuring. Do not exceed 10 grams/dose.] | 10.0 | 1 full packet
- Administer VISTOGARD as soon as possible after an overdose or early-onset toxicity within 96 hours following the end of fluorouracil or capecitabine administration.
- Administer full course of VISTOGARD (20 doses) as directed.

2.2 Preparation and Administration

- Mix each VISTOGARD dose with 3 to 4 ounces of soft foods such as applesauce, pudding or yogurt and ingest within 30 minutes. Do not chew the VISTOGARD granules. Drink at least 4 ounces of water.
- If a patient vomits within 2 hours of taking a dose of VISTOGARD, initiate another complete dose as soon as possible after the vomiting episode. Administer the next dose at the regularly scheduled time.
- If a patient misses a dose at the scheduled time, administer that dose of VISTOGARD as soon as possible. Administer the next dose at the regularly scheduled time.
- Administer VISTOGARD via a nasogastric tube (NG tube) or gastrostomy tube (G-Tube) when necessary (eg, severe mucositis or coma). Follow the instructions below for each dose administration:
  1. Prepare approximately 4 fluid ounces (about 100 mL) of a food starch-based thickening product in water and stir briskly until the thickener has dissolved.
  2. Crush the contents of one full 10 gram packet of VISTOGARD granules to a fine powder.
  3. Add the crushed VISTOGARD granules to 4 ounces (about 100 mL) of the reconstituted food starch-based thickening product. For pediatric patients receiving less than 10 grams, prepare the mixture at a ratio of no greater than 1 gram per 10 mL of reconstituted food starch-based thickening product and mix thoroughly.
  4. After administration of the mixture using the NG tube or G-Tube, flush the tube with water.

3 DOSAGE FORMS AND STRENGTHS

Oral granules: 10 grams of orange-flavored, white-to-off-white, oral granules (95% w/w) in single-dose packets.

4 CONTRAINDICATIONS

None.

5 WARNINGS AND PRECAUTIONS

None.

6 ADVERSE REACTIONS

6.1 Clinical Trials Experience

Because clinical trials are conducted under widely varying conditions and using a wide range of doses, adverse reaction rates observed in the clinical trials of a drug cannot be directly compared to rates in the clinical trials of another drug and may not reflect the rates observed in practice.

The safety of VISTOGARD was assessed in 135 patients (median age 59 years, 56% male) treated in 2 single-arm, open-label, multi-center trials. VISTOGARD was administered at 10 grams orally every 6 hours for 20 doses or at a body surface area adjusted dosage of 6.2 grams/m^2/dose for 20 doses in four patients between 1 and 7 years of age. The median duration of exposure was 4.8 days, with a median of 20 doses (range 1 to 23). VISTOGARD was discontinued for adverse reactions in two (1.4%) patients. Serious adverse reactions and Grade ≥3 adverse reactions were seen in one patient receiving VISTOGARD (Grade 3 nausea and vomiting). Table 2 summarizes the adverse reactions that occurred in greater than 2% of patients in Studies 1 and 2 combined.

Table 2 Adverse Reactions in > 2% of Patients Receiving VISTOGARD in Studies 1 and 2
Adverse Reaction | N=135 Patients
Vomiting | 13 (10%)
Nausea | 7 (5%)
Diarrhea | 4 (3%)

8 USE IN SPECIFIC POPULATIONS

8.1 Pregnancy

Risk Summary

Limited case reports of uridine triacetate use during pregnancy are insufficient to inform a drug-associated risk of birth defects and miscarriage. When administered orally to pregnant rats during the period of organogenesis, uridine triacetate at doses of one-half the maximum recommended human dose (MRHD) of 40 grams per day was not teratogenic and did not produce adverse effects on embryo-fetal development [see Data] .

The background risk of major birth defects and miscarriage for the indicated population are unknown. In the U.S. general population, the estimated background risk of major birth defects and miscarriage in clinically recognized pregnancies is 2% to 4% and 15% to 20%, respectively.

Data

Animal Data

In an embryo-fetal development study, uridine triacetate was administered orally to pregnant rats during the period of organogenesis at doses up to 2000 mg/kg per day (about one-half the maximum recommended human dose (MRHD) of 40 grams per day on a body surface area basis). There was no evidence of teratogenicity or harm to the fetus and no effect on maternal body weight and overall health.

8.2 Lactation

Risk Summary

There are no data on the presence of uridine triacetate in human milk, the effect on the breastfed infant or the effect on milk production. The development and health benefits of breastfeeding should be considered along with the mother's clinical need for VISTOGARD and any potential adverse effects on the breastfed infant from VISTOGARD or from the underlying maternal condition.

8.4 Pediatric Use

The safety and effectiveness of VISTOGARD have been established in pediatric patients. Use of VISTOGARD in pediatric patients is supported by an open-label clinical study of adults (Study 1) and a second open-label clinical study which included 6 pediatric patients ranging in age from 1 to 16 years (Study 2). Four of these pediatric patients were between 1 to 7 years of age and received a body-surface area adjusted dosage of 6.2 grams/m^2/dose for 20 doses. The clinical response and safety in adult and pediatric patients treated with VISTOGARD were similar; however, clinical data are limited [see Clinical Studies (14)].

8.5 Geriatric Use

Of the 135 patients in clinical studies with VISTOGARD, 30% were 65 and over, including 11% that were 75 and over. Clinical studies of VISTOGARD did not include sufficient numbers of subjects aged 65 and over to determine whether they respond differently from younger subjects.

11 DESCRIPTION

VISTOGARD oral granules contain the active ingredient uridine triacetate which is a pyrimidine analog. The chemical name for uridine triacetate is (2',3',5'-tri-O-acetyl-β-D-ribofuranosyl)-2,4(1H,3H)-pyrimidinedione. The molecular weight is 370.3 grams/mole and it has an empirical formula of C15H18N2O9. The structural formula is:

Each single-dose 10 gram packet of VISTOGARD orange-flavored oral granules (95% w/w) contains 10 grams of uridine triacetate and the following inactive ingredients: ethylcellulose (0.309 grams), Opadry®Clear [proprietary dispersion of hydroxypropylmethylcellulose and Macrogol] (0.077 grams), and natural orange juice flavor (0.131 grams).

12 CLINICAL PHARMACOLOGY

12.1 Mechanism of Action

Uridine triacetate is an acetylated pro-drug of uridine. Following oral administration, uridine triacetate is deacetylated by nonspecific esterases present throughout the body, yielding uridine in the circulation. Uridine competitively inhibits cell damage and cell death caused by fluorouracil.

Fluorouracil is a cytotoxic antimetabolite that interferes with nucleic acid metabolism in normal and cancer cells. Cells anabolize fluorouracil to the cytotoxic intermediates 5-fluoro-2'-deoxyuridine-5'-monophosphate (FdUMP) and 5-fluorouridine triphosphate (FUTP). FdUMP inhibits thymidylate synthase, blocking thymidine synthesis. Thymidine is required for DNA replication and repair. Uridine is not found in DNA.

The second source of fluorouracil cytotoxicity is the incorporation of its metabolite, FUTP, into RNA. This incorporation of FUTP into RNA is proportional to systemic fluorouracil exposure. Excess circulating uridine derived from VISTOGARD is converted into uridine triphosphate (UTP), which competes with FUTP for incorporation into RNA.

12.3 Pharmacokinetics

Absorption

VISTOGARD delivers 4- to 6-fold more uridine into the systemic circulation compared to equimolar doses of uridine itself. Maximum concentrations of uridine in plasma following oral VISTOGARD are generally achieved within 2 to 3 hours, and the half-life ranges from approximately 2 to 2.5 hours.

Studies 1 and 2 included an assessment of plasma uridine in a subgroup of patients who were overdosed with fluorouracil or experiencing early-onset of serious fluorouracil toxicities. Samples were obtained prior to VISTOGARD treatment and at 1 to 4 hours following the first and final doses of VISTOGARD given at 10 g (adults) or 6.2 grams/m^2(pediatric) every 6 hours for up to 20 doses. Plasma uridine concentrations are summarized in Table 3.

Table 3 Plasma Uridine Concentrations (µM) in Studies 1 and 2
Study | Predose | Post First Dose | Post Final Dose
Study 1 [Values shown are mean (standard deviation) for plasma uridine (µM)] | 8 (33) | 99 (64) | 160 (81)
Study 1 [Values shown are mean (standard deviation) for plasma uridine (µM)] | N = 49 | N = 49 | N = 40
Study 2 | 5 (17) | 119 (59) | 153 (68)
Study 2 | N = 27 | N = 26 | N = 24

Food Effect on Uridine PK:A study in healthy adult subjects receiving a slightly different formulation of uridine triacetate granules (6 gram dose) under fed and fasted conditions showed no difference in the overall rate and extent of uridine exposure.

Distribution

Circulating uridine is taken up into mammalian cells via specific nucleoside transporters, and also crosses the blood brain barrier.

Excretion

Uridine can be excreted via the kidneys, but is also metabolized by normal pyrimidine catabolic pathways present in most tissues.

Drug Interaction Studies

In vitroenzyme inhibition data did not reveal meaningful inhibitory effects of uridine triacetate or uridine on CYP3A4, CYP1A2, CYP2C8, CYP2C9, CYP2C19, CYP2D6, and CYP2E1. In vitroenzyme induction data did not reveal an inducing effect of uridine triacetate or uridine on CYP1A2, CYP2B6, or CYP3A4.

In vitrodata showed that uridine triacetate was a weak substrate for P-glycoprotein. Uridine triacetate inhibited the transport of a known P-glycoprotein substrate, digoxin, with an IC50 of 344 µM. Due to the potential for high local (gut) concentrations of the drug after dosing, the interaction of VISTOGARD with orally administered P-gp substrate drugs cannot be ruled out.

In vivodata in humans are not available.

Specific Populations

Sex

Pharmacokinetics analyses showed that sex did not have a significant effect on uridine pharmacokinetics.

Age

Pharmacokinetic analysis showed that within the age range evaluated (20 to 83 years), age did not have a significant effect on uridine pharmacokinetics.

Body Size

Pharmacokinetic analyses showed no clinically meaningful effect of body surface area on uridine PK in adults.

13 NONCLINICAL TOXICOLOGY

13.1 Carcinogenesis, Mutagenesis, Impairment of Fertility

Long-term studies in animals have not been performed to evaluate the carcinogenic potential of uridine triacetate.

Uridine triacetate was not genotoxic in the Ames test, the mouse lymphoma assay and the mouse micronucleus test.

Orally administered uridine triacetate did not affect fertility or general reproductive performance in male and female rats at doses up to 2000 mg/kg per day (about one-half the maximum recommend human dose (MRHD) of 40 grams per day on a body surface area basis).

13.2 Animal Toxicology and/or Pharmacology

In mice given a sub-lethal dose of fluorouracil, the administration of oral uridine triacetate diminished hematological toxicity as a function of increasing dose, but did not completely prevent hematological toxicity. In mice given a lethal dose of fluorouracil, administration of oral uridine triacetate increased survival to 90% when given within 24 hours. Survival diminished with increasing interval between the fluorouracil dose and uridine triacetate treatment demonstrating that earlier administration of uridine triacetate is more beneficial. In similar experiments in mice, uridine triacetate treatment diminished damage to the intestinal mucosa caused by fluorouracil treatment.

14 CLINICAL STUDIES

The efficacy of VISTOGARD was assessed in 135 patients who were treated in two open-label trials, Study 1 (n=60) and Study 2 (n=75). The patients in both studies had either received an overdose of fluorouracil or capecitabine, or presented with severe or life-threatening toxicities within 96 hours following the end of fluorouracil or capecitabine administration. Overdose was defined as administration of fluorouracil at a dose, or infusion rate, greater than the intended dose or maximum tolerated dose for the patient's intended regimen of fluorouracil. VISTOGARD was administered at 10 grams orally every 6 hours for 20 doses or at a body surface area adjusted dosage of 6.2 grams/m^2/dose for 20 doses for four patients between 1 and 7 years of age. The major efficacy outcome was survival at 30 days or until the resumption of chemotherapy if prior to 30 days.

In Study 1 and Study 2 combined, the median age of the patients was 59 years (range: 1 to 83), 56% were male, 72% were white, 9% were Black/African American, 6% were Hispanic, 4% were Asian, and 95% had a cancer diagnosis. Of the 135 patients, 117 were treated with VISTOGARD following an overdose of fluorouracil (n=112) or capecitabine (n=5), and 18 were treated after exhibiting severe or life-threatening fluorouracil toxicities within 96 hours following the end of fluorouracil administration. The severe or life-threatening toxicities involved the central nervous system (such as encephalopathy, acute mental status change), cardiovascular system, gastrointestinal system (such as mucositis), and bone marrow. A total of six pediatric patients were administered VISTOGARD. Four patients initiated VISTOGARD more than 96 hours following the end of fluorouracil or capecitabine administration. Of the 112 patients overdosed with fluorouracil, 105 (94%) were overdosed by infusion rate only (range 1.3 to 720 times the planned infusion rate), four (4%) were overdosed by dose only, and three (3%) were overdosed by both dose and rate.

The survival results are shown in Table 4. Of the 135 patients who were treated with VISTOGARD in Studies 1 and 2 there were five deaths due to fluorouracil or capecitabine toxicity (4%). Of the five patients who died, two were treated after 96 hours following the end of fluorouracil administration. In the patients treated with VISTOGARD for an overdose of fluorouracil or capecitabine in Studies 1 and 2 combined (n=117), survival at 30 days was 97% (n=114). In the patients receiving VISTOGARD for early-onset severe or life-threatening toxicity in Studies 1 and 2 combined (n=18), the survival at 30 days was 89% (n=16). In these studies 33% of patients (n=45) resumed chemotherapy in less than 30 days. Based on retrospective historical case reports of 25 patients who were overdosed with fluorouracil and received supportive care only, all were overdosed by rate with a range 1.9 to 64 times the planned infusion rate, and 84% died.

Table 4 Combined Efficacy: All Patients in Study 1 and Study 2
 | Overdose | Early-Onset | Overall
Total Enrolled | 117 | 18 | 135
Survival [Survival includes patients who survived at 30 days or patients who resumed chemotherapy prior to 30 days.] | 114 (97%) | 16 (89%) | 130 (96%)
Death | 3 (3%) | 2 (11%) | 5 (4%)

16 HOW SUPPLIED/STORAGE AND HANDLING

VISTOGARD orange-flavored oral granules (95% w/w) are available in single-dose packets containing 10 grams of uridine triacetate.

NDC Number | Package Configuration
50633-220-20 | Course of therapy package:
 | 1 carton containing 20 single-dose packets of VISTOGARD
50633-220-04 | 24-Hour Pack:
 | 1 carton containing 4 single-dose packets of VISTOGARD

STORAGE AND HANDLING

Store at USP controlled room temperature, 25°C (77°F); excursions permitted to 15° to 30 °C (59° to 86°F).

17 PATIENT COUNSELING INFORMATION

Advise the patient or caregiver to read the FDA-approved patient labeling (Patient Information)

Dosing Instructions [see Dosage and Administration (2.1)and (2.2)]

Advise the patient or caregiver:

- The importance of taking all 20 doses, even if they feel well.
- That VISTOGARD can be taken mixed in food (applesauce, pudding or yogurt).
- That the VISTOGARD granules should not be chewed.
- That if the patient vomits within 2 hours of taking a dose of VISTOGARD to take another complete dose as soon as possible after vomiting. Take the next dose at the regularly scheduled time.
- That if the patient misses a dose at the scheduled time, to take that dose of VISTOGARD as soon as possible. Then take the next dose at the regularly scheduled time.

Manufactured for and distributed by:

BTG International Inc.
West Conshohocken, PA, 19428

BTG
Pharmaceuticals
a SERB company

VISTOGARD®is a registered trademark of BTG International Inc.
The SERB logo is a registered trademark of SERB S.à.r.l.

Patient Information
VISTOGARD (VIS-toe-gard)
(uridine triacetate)
oral granules

What is VISTOGARD?

VISTOGARD is a prescription medicine that contains uridine, a substance that is normally found in your body. VISTOGARD is used for emergency treatment of adults and children:

- after an overdose of fluorouracil or capecitabine with or without symptoms, or
- who have early signs of severe or life-threatening side effects that affect the heart, or early signs of severe or life threatening neurologic (central nervous system) problems, or certain unusually severe side effects within 4 days (96 hours) after receiving treatment with fluorouracil or capecitabine

VISTOGARD should only be used for the emergency treatment of side effects of fluorouracil or capecitabine, because it may decrease the effectiveness of these medicines.

It is not known if VISTOGARD is safe and effective if started more than 4 days (96 hours) after the end of a dose of fluorouracil or capecitabine.

Before taking VISTOGARD, tell your healthcare provider about all your medical conditions, including if you:

- are pregnant or plan to become pregnant. It is not known if VISTOGARD will harm your unborn baby.
- are breastfeeding or plan to breastfeed. It is not known if VISTOGARD passes into your breast milk. Talk to your healthcare provider about the best way to feed your baby if you take VISTOGARD.

Tell your healthcare provider about all the medicines you take,including prescription and over-the-counter medicines, vitamins, and herbal supplements.

How should I take VISTOGARD?

- Take VISTOGARD exactly as prescribed by your healthcare provider.
- It is important that you take all 20 doses of VISTOGARD even if you feel well.
- VISTOGARD comes in single-dose packets that contain 10 grams of orange-flavored granules.
- If your healthcare provider decides that you can give VISTOGARD to your child at home, it is important that you follow your healthcare provider's instructions. Your healthcare provider will prescribe VISTOGARD to your child based on your child's weight.
- The usual adult dose of VISTOGARD is 1 packet taken by mouth every 6 hours for a total of 20 doses.
- If you vomit within 2 hours of taking a dose of VISTOGARD, take another full dose as soon as possible. Then take your next VISTOGARD dose at your next regularly scheduled time.
- If you miss a dose of VISTOGARD at the scheduled time, take the missed dose as soon as possible. Then take the next dose at the regularly scheduled time.

Preparing and taking a dose of VISTOGARD:

- Mix each packet of VISTOGARD granules with 3 to 4 ounces of soft food such as applesauce, pudding or yogurt in a small container.
- Take all of the VISTOGARD granules mixed with food within 30 minutes of mixing.
- Do not chew the VISTOGARD granules.
- Drink at least 4 ounces of water to make sure that you swallow all of the medicine.

What are the possible side effects of VISTOGARD?

Common side effects of VISTOGARD include: vomiting, nausea, and diarrhea.

These are not all the possible side effects of VISTOGARD.

Call your doctor for medical advice about side effects. You may report side effects to FDA at 1-800-FDA-1088.

How should I store VISTOGARD?

- Store VISTOGARD at room temperature between 68°F to 77°F (20°C to 25°C)

Keep VISTOGARD and all medicines out of the reach of children.

General information about the safe and effective use of VISTOGARD.

Medicines are sometimes prescribed for purposes other than those listed in a Patient Information leaflet. Do not use VISTOGARD for a condition for which it was not prescribed. Do not give VISTOGARD to other people, even if they have the same symptoms that you have. It may harm them. You can ask your pharmacist or healthcare provider for information about VISTOGARD that is written for health professionals.

What are the ingredients of VISTOGARD?

Active Ingredient:uridine triacetate

Inactive Ingredients:ethylcellulose, Opadry Clear [proprietary dispersion of hydroxypropylmethylcellulose and Macrogol], and natural orange juice flavor.

Manufactured for an distributed by: BTG International Inc., West Conshohocken, PA, 19428

BTGPharmaceutical
a SERB company

VISTOGARD®is a registered trademark of BTG International Inc.
The SERB logo is a registered trademark of SERB S.à.r.l.

For more information, go to www.vistogard.com or call 1-877-377-3784

This Patient Information has been approved by the U.S. Food and Drug Administration

Issued: 10/2023

PRINCIPAL DISPLAY PANEL - 20 Count - 10 g Packet Carton

NDC 50633-220-20
Rx Only

VISTOGARD®10 g
(uridine triacetate) oral granules

Carton contains 20 x 10 gram packets

BTG
Pharmaceuticals

PRINCIPAL DISPLAY PANEL - 4 Count 10 g Packet Carton

NDC 50633-220-04
Rx Only

VISTOGARD®10 g
(uridine triacetate) oral granules

Carton contains 4 x 10 gram packets

BTG
Pharmaceuticals

PRINCIPAL DISPLAY PANEL - 10 g Single Dose Sachet Foil

NDC 50633-220-10
Rx Only

VISTOGARD®10 g
(uridine triacetate) oral granules

Single-Dose Packets

BTG
Pharmaceuticals